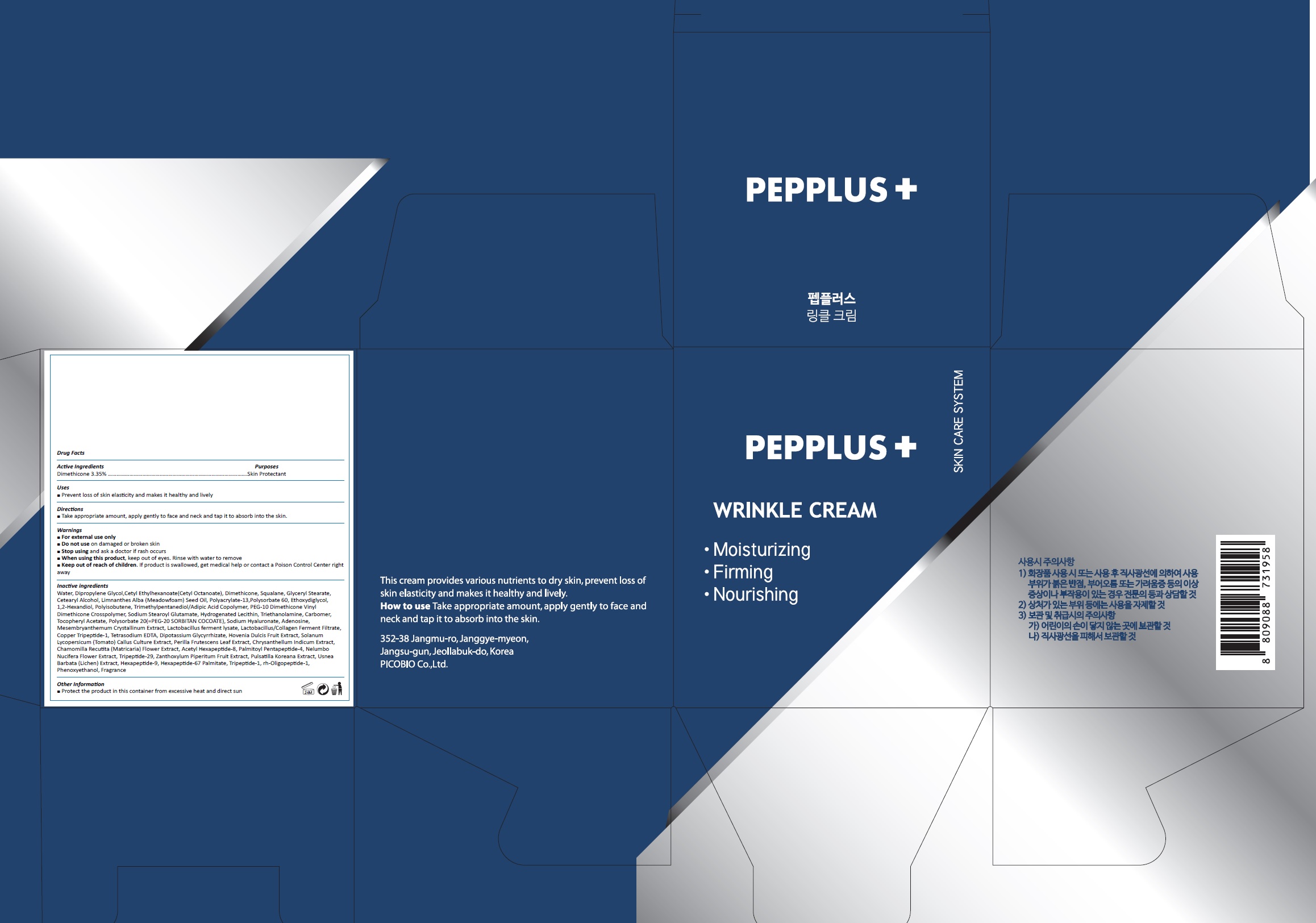 DRUG LABEL: PEPPLUS WRINKLE
NDC: 72211-011 | Form: CREAM
Manufacturer: Picobio Co., Ltd
Category: otc | Type: HUMAN OTC DRUG LABEL
Date: 20211102

ACTIVE INGREDIENTS: DIMETHICONE 1.675 g/50 g
INACTIVE INGREDIENTS: WATER; CETYL ETHYLHEXANOATE; SQUALANE; GLYCERYL MONOSTEARATE; CETOSTEARYL ALCOHOL; MEADOWFOAM SEED OIL; POLYACRYLAMIDE (1500 MW); POLYSORBATE 60; DIETHYLENE GLYCOL MONOETHYL ETHER

72211-011 PEPPLUS WRINKLE CREAM

ACTIVE INGREDIENT

Dimethicone 3.35%

PURPOSE

Skin Protectant

INDICATIONS AND USAGE

Prevent loss of skin elasticity and makes it healthy and lively

DOSAGE AND ADMINISTRATION

 Take appropriate amount, apply gently to face and neck and tap it to absorb into the skin.

WARNINGS

For external use only.
Do not use on damaged or broken skin.
When using this product, keep out of eyes. Rinse with water to remove.
Stop using and ask a doctor if rash occurs.

KEEP OUT OF REACH OF CHILDREN

Keep out of reach of the children. If product is swallowed, get medical help or contact a poison control center right away.

INACTIVE INGREDIENT

Water, Dipropylene Glycol, Cetyl Ethylhexanoate, Squalane, Glyceryl Stearate,, Cetearyl Alcohol, Limnanthes Alba (Meadowfoam) Seed Oil, Polyacrylate-13, Polysorbate 60, Ethoxydiglycol, Sodium Hyaluronate, Trimethylpentanediol/Adipic Acid Copolymer, Sodium Stearoyl Glutamate, Hydrogenated Lecithin, Perilla Frutescens Leaf Extract, Nelumbo Nucifera Flower Extract, Chrysanthellum Indicum Extract, Chamomilla Recutita (Matricaris) Flower Extract, Hovenia Dulcis Fruit Extract, Solanum Lycopersicum (Tomato) Fruit/Leaf/Stem Extract, Lactobacillus ferment lysate, Mesembryanthemum Crystallinum Extract, Lactobacillus/Collagen Ferment Filtrate, 1,2-Hexanediol, Phenoxyethanol, PEG-10 Dimethicone/Vinyl Dimethicone Crosspolymer, Polyisobutene, Polysorbate 20, Carbomer, Triethanolamine, Adenosine, Tetrasodium EDTA, Tocopheryl Acetate, Dipotassium Glycyrrhizate, Copper Tripeptide-1, Acetyl Hexapeptide-8, Palmitoyl Pentapeptide-4, Tripeptide-1, Tripeptide-29, Hexapeptide-9, Hexapeptide-67 Palmitate, rh-Oligopeptide-1, Perfume